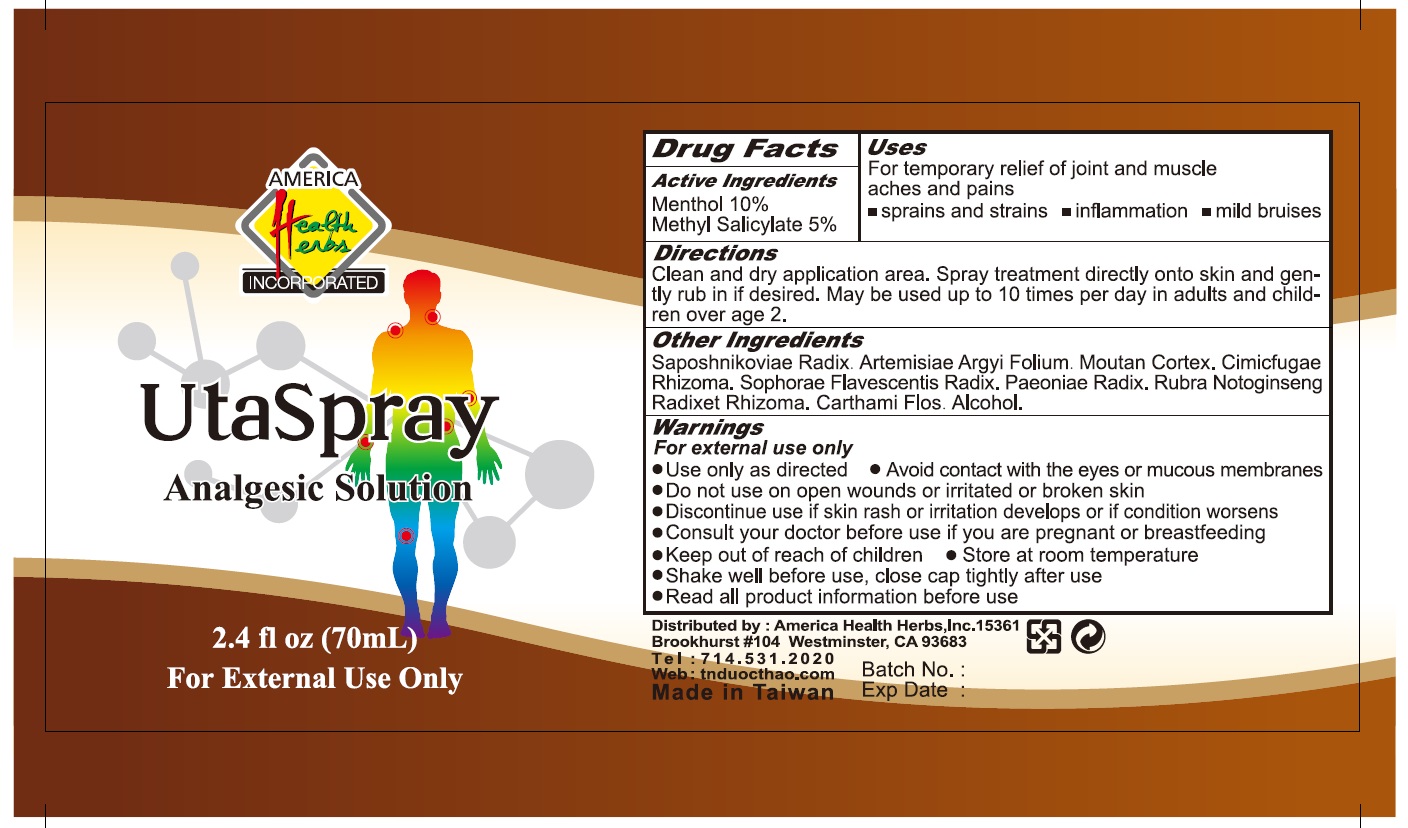 DRUG LABEL: UtaSpray
NDC: 82198-0008 | Form: LIQUID
Manufacturer: Big 5 Nutrition LLC
Category: otc | Type: HUMAN OTC DRUG LABEL
Date: 20231121

ACTIVE INGREDIENTS: MENTHOL 100 mg/1 mL; METHYL SALICYLATE 50 mg/1 mL
INACTIVE INGREDIENTS: SAPOSHNIKOVIA DIVARICATA ROOT; ARTEMISIA ARGYI LEAF; PAEONIA X SUFFRUTICOSA ROOT BARK; ACTAEA CIMICIFUGA ROOT; SOPHORA FLAVESCENS ROOT; PAEONIA LACTIFLORA ROOT; PANAX NOTOGINSENG ROOT; SAFFLOWER; ALCOHOL

UtaSpray

Active Ingredients

Menthol 10%

Methyl Salicylate 5%

Purpose

External analgesic

Uses

For temporary relief of joint and muscle aches and pains

- sprains and strains
- inflammation
- mild bruises

Warnings

For external use only

- Use only as directed
- Avoid contact with the eyes or mucous membranes
- Do not use on open wounds or irritated or broken skin
- Discontinue use if skin rash or irritation develops or if condition worsens
- Consult your doctor before use if you are pregnant or breastfeeding

- Keep out of reach of children

- Store at room temperature
- Shake well before use, close cap tightly after use
- Read all product information before use

Directions

- Clean and dry application area. Spray treatment directly onto skin and gently rub in if desired. May be used up to 10 times per day in adults and children over age 2.

Other Ingredients

Saposhnikoviae Radix, Artemisiae Argyi Folium, Moutan Cortex, Cimicfugae Rhizoma, Sophorae Flavescentis Radix, Paeoniae Radix, Rubra Notoginseng Radixet Rhizoma, Carthami Flos, Alcohol.